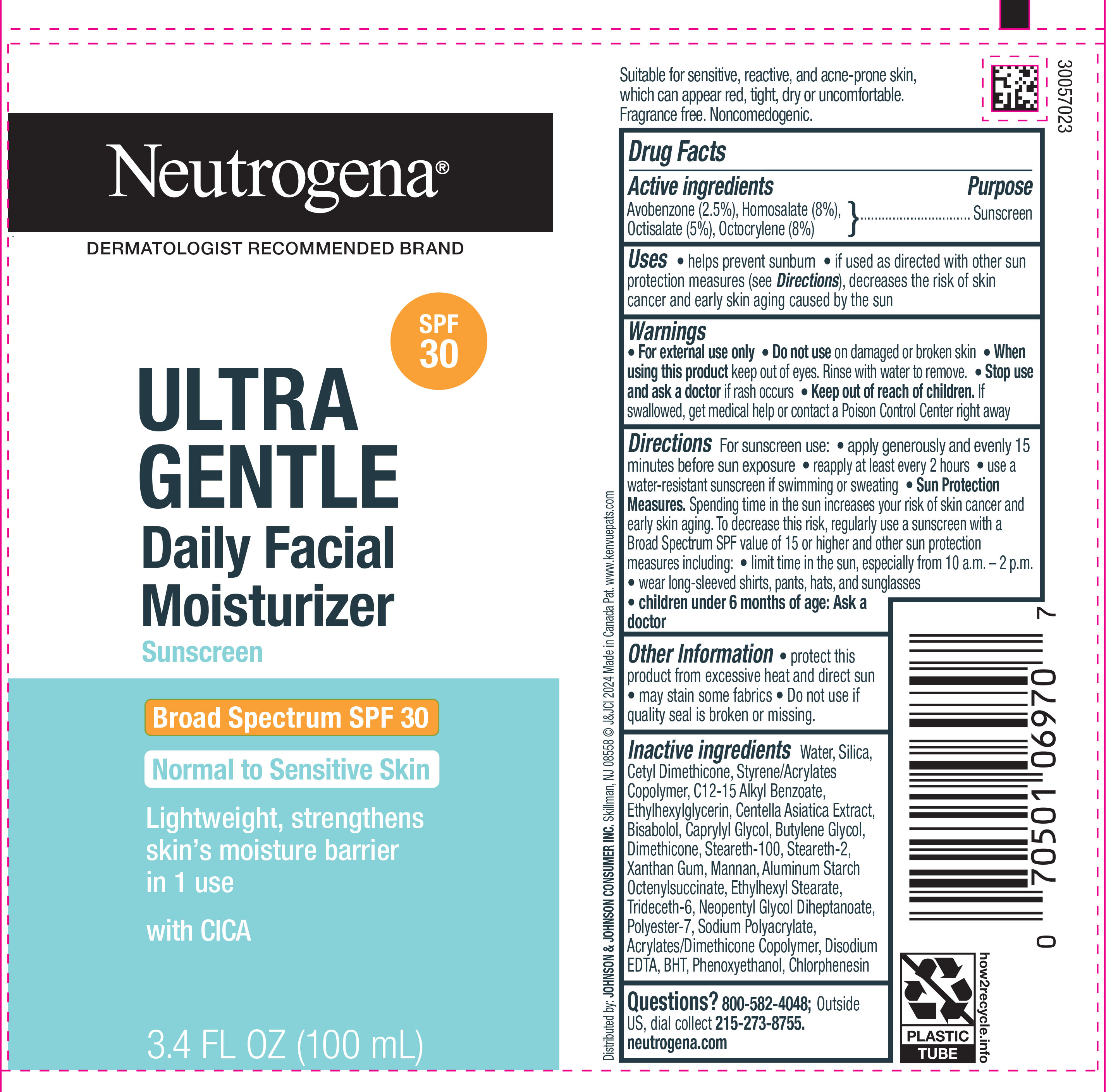 DRUG LABEL: Neutrogena Ultra Gentle Daily Facial Moisturizer Sunscreen Broad Spectrum SPF 30
NDC: 69968-0890 | Form: LOTION
Manufacturer: Kenvue Brands LLC
Category: otc | Type: HUMAN OTC DRUG LABEL
Date: 20250917

ACTIVE INGREDIENTS: HOMOSALATE 80 mg/1 mL; OCTOCRYLENE 80 mg/1 mL; OCTISALATE 50 mg/1 mL; AVOBENZONE 25 mg/1 mL
INACTIVE INGREDIENTS: CETYL DIMETHICONE 25; BUTYL METHACRYLATE/METHYL METHACRYLATE/METHACRYLIC ACID/STYRENE CROSSPOLYMER; PHENOXYETHANOL; WATER; DIMETHICONE; MANNAN; CENTELLA ASIATICA TRITERPENOIDS; ETHYLHEXYLGLYCERIN; LEVOMENOL; XANTHAN GUM; BUTYLENE GLYCOL; ALUMINUM STARCH OCTENYLSUCCINATE; C12-15 ALKYL BENZOATE; CAPRYLYL GLYCOL; STEARETH-2; POLYESTER-7; 2-ETHYLHEXYL ACRYLATE, METHACRYLATE, METHYL METHACRYLATE, OR BUTYL METHACRYLATE/HYDROXYPROPYL DIMETHICONE COPOLYMER (30000-300000 MW); EDETATE DISODIUM; STEARETH-100; ETHYLHEXYL STEARATE; NEOPENTYL GLYCOL DIHEPTANOATE; BHT; CHLORPHENESIN; TRIDECETH-6; SILICON DIOXIDE

Neutrogena Ultra Gentle Daily Facial Moisturizer Sunscreen Broad Spectrum SPF 30

Drug Facts

Active ingredients

Avobenzone (2.5%), Homosalate (8%), Octisalate (5%), Octocrylene (8%)

Purpose

Sunscreen

Uses

- helps prevent sunburn
  - if used as directed with other sun protection measures (see Directions), decreases the risk of skin cancer and early skin aging caused by the sun

Warnings

- For external use only

- Do not use on damaged or broken skin

- When using this product keep out of eyes. Rinse with water to remove.

- Stop use and ask a doctor if rash occurs

- Keep out of reach of children. If swallowed, get medical help or contact a Poison Control Center right away.

Directions

For sunscreen use: apply generously and evenly 15 minutes before sun exposure

- reapply at least every 2 hours
- use a water-resistant sunscreen if swimming or sweating
  - Sun Protection Measures. Spending time in the sun increases your risk of skin cancer and early skin aging. To decrease this risk, regularly use a sunscreen with a Broad Spectrum SPF value of 15 or higher and other sun protection measures including:

limit time in the sun, especially from 10 a.m. – 2 p.m.

wear long-sleeved shirts, pants, hats, and sunglasses

- children under 6 months of age: Ask a doctor

Other information

- protect this product from excessive heat and direct sun
- may stain some fabrics
- Do not use if quality seal is broken or missing

Inactive ingredients

Water, Silica, Cetyl Dimethicone, Styrene/Acrylates Copolymer, C12-15 Alkyl Benzoate, Ethylhexylglycerin, Centella Asiatica Extract, Bisabolol, Caprylyl Glycol, Butylene Glycol, Dimethicone, Steareth-100, Steareth-2, Xanthan Gum, Mannan, Aluminum Starch Octenylsuccinate, Ethylhexyl Stearate, Trideceth-6, Neopentyl Glycol Diheptanoate, Polyester-7, Sodium Polyacrylate, Acrylates/Dimethicone Copolymer, Disodium EDTA, BHT, Phenoxyethanol, Chlorphenesin

Questions?

800-582-4048; Outside US, dial collect 215-273-8755. neutrogena.com

Distributed by:
JOHNSON & JOHNSON CONSUMER INC.
Skillman, NJ 08558

PRINCIPAL DISPLAY PANEL - 100 mL Tube

Neutrogena®

DERMATOLOGIST RECOMMENDED BRAND

SPF

30

ULTRA

GENTLE

Daily Facial

Moisturizer

Sunscreen

Broad Spectrum SPF 30

Normal to Sensitive Skin

Lightweight, strengthens

skin’s moisture barrier

in 1 use

with CICA

3.4 FL OZ (100 mL)